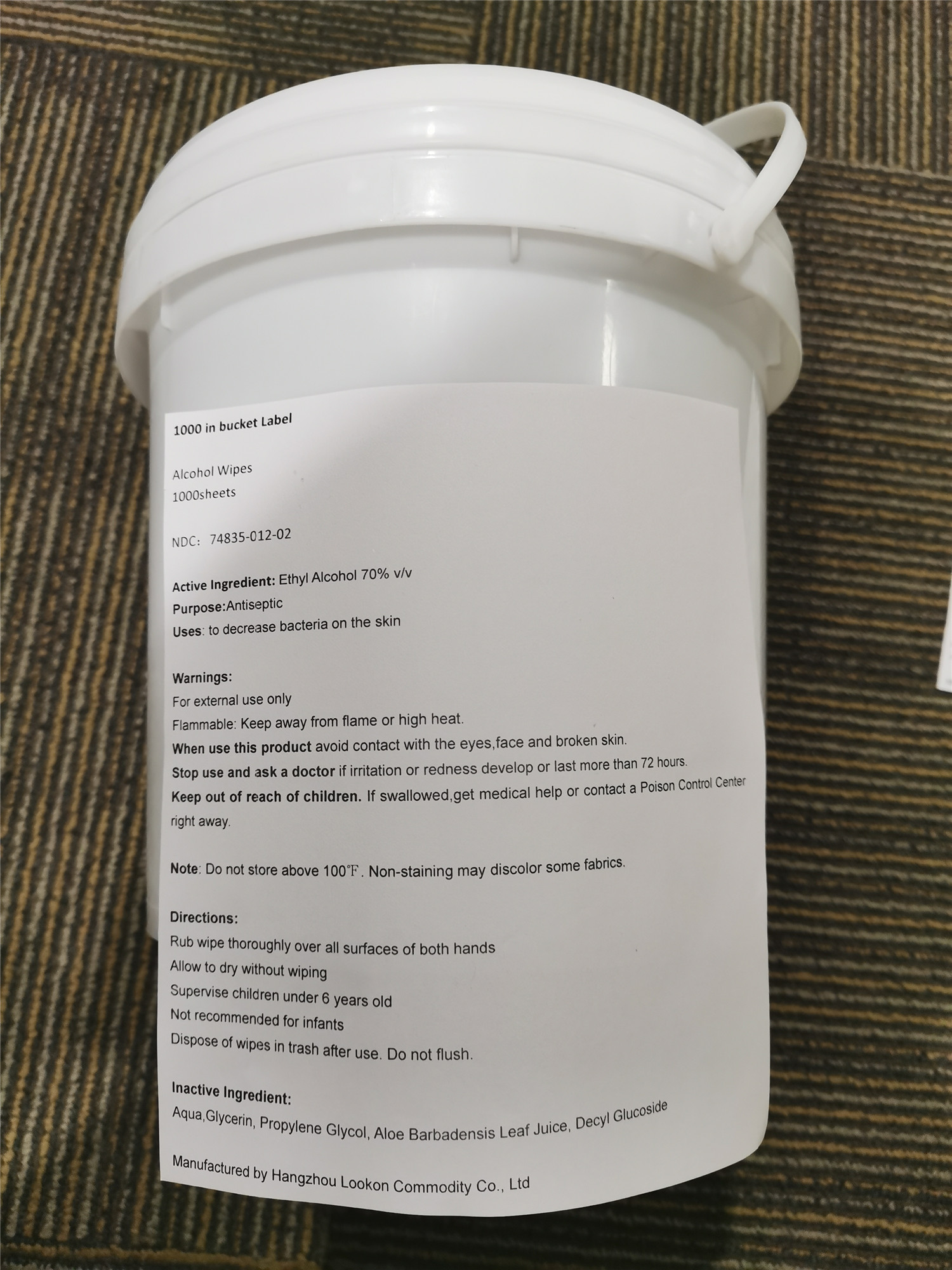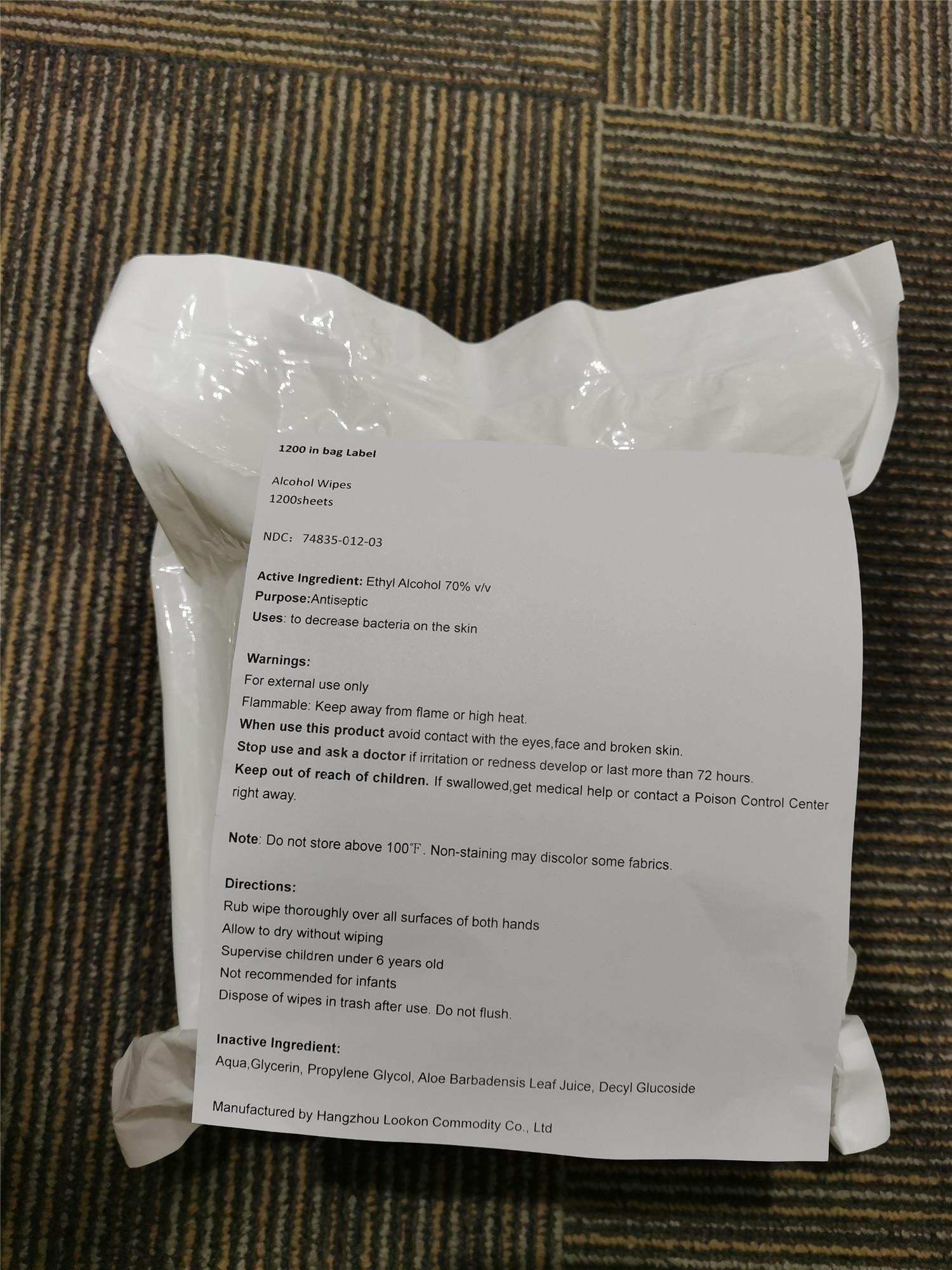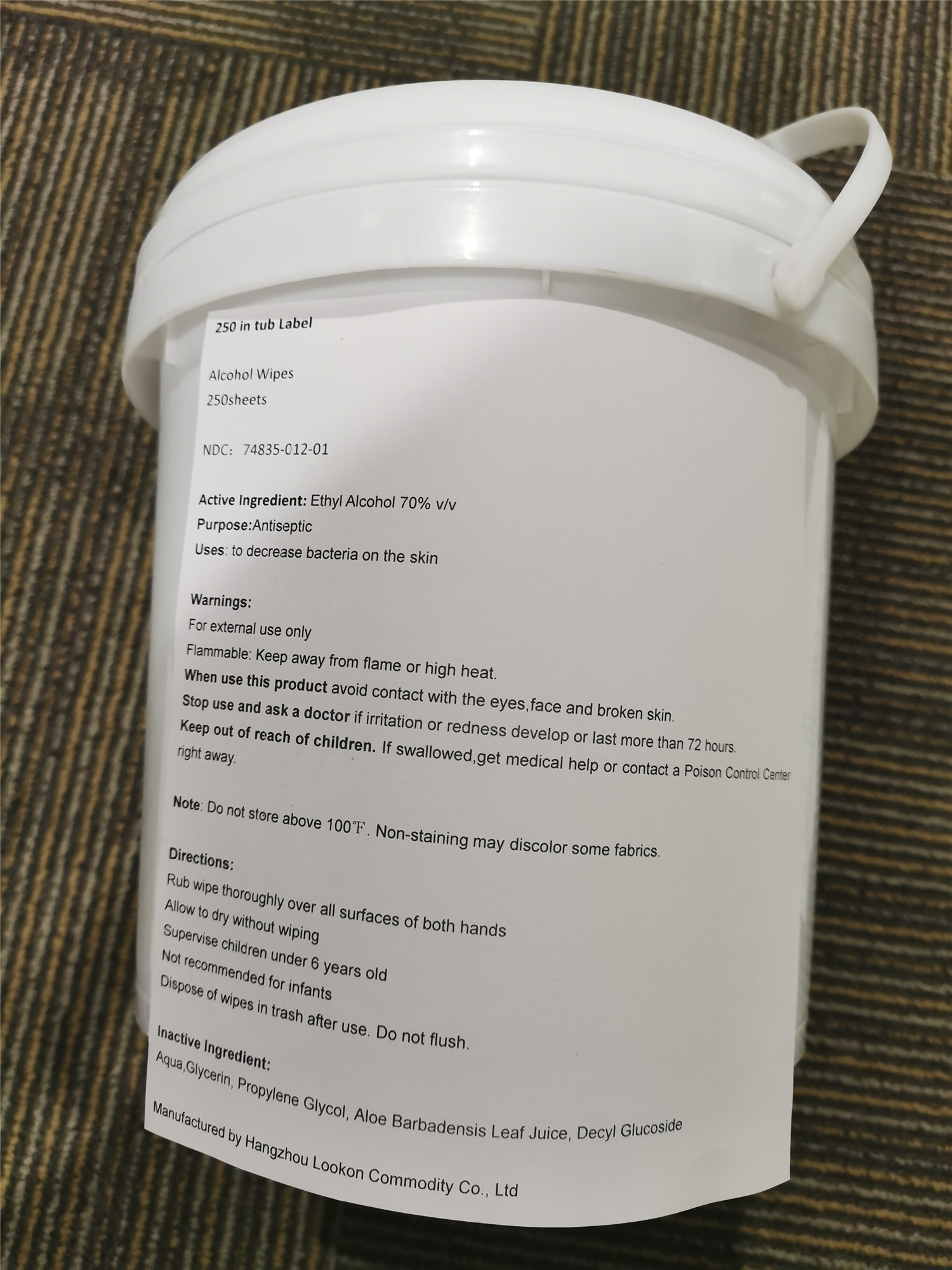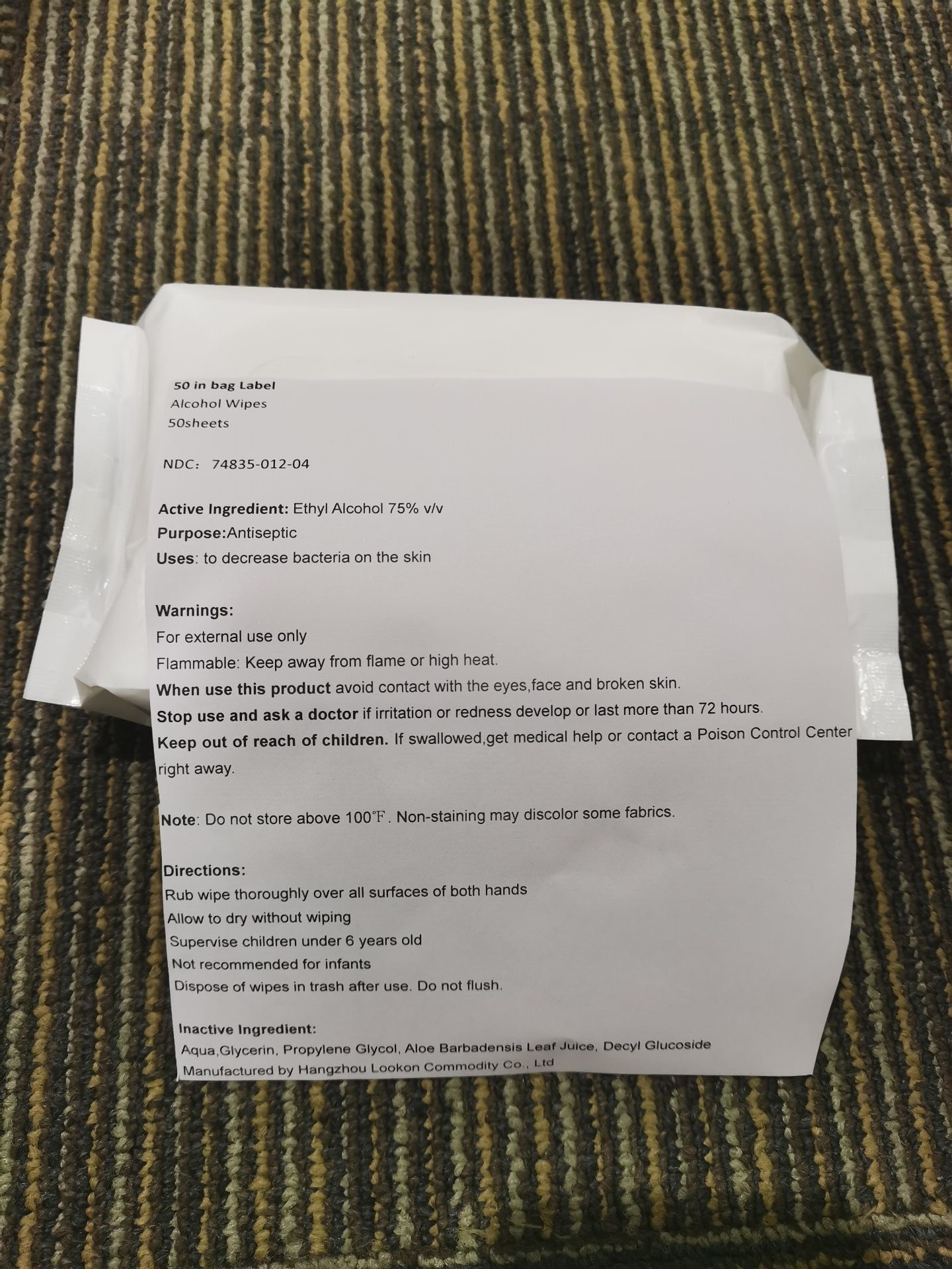 DRUG LABEL: Alcohol Wipes
NDC: 74835-012 | Form: CLOTH
Manufacturer: Hangzhou Lookon Commodity Co., Ltd.
Category: otc | Type: HUMAN OTC DRUG LABEL
Date: 20221018

ACTIVE INGREDIENTS: ALCOHOL 70 mL/100 mL
INACTIVE INGREDIENTS: GLYCERIN; PROPYLENE GLYCOL; ALOE VERA LEAF; DECYL GLUCOSIDE; WATER

Alcohol Wipes

Active Ingredient: Ethyl Alcohol 70% v/v

Purpose:Antiseptic

INDICATIONS AND USAGE

Uses: to decrease bacteria on the skin

Warnings:

For external use only

Flammable: Keep away from flame or high heat.

When use this product avoid contact with the eyes,face and broken skin.

Stop use and ask a doctor if irritation or redness develop or last more than 72 hours.

Keep out of reach of children. If swallowed,get medical help or contact a Poison Control Center right away.

WHEN USING

When use this product avoid contact with the eyes,face and broken skin.

Stop use and ask a doctor if irritation or redness develop or last more than 72 hours.

Keep out of reach of children. If swallowed,get medical help or contact a Poison Control Center right away.

STORAGE AND HANDLING

Note: Do not store above 100℉. Non-staining may discolor some fabrics.

Directions:

Rub wipe thoroughly over all surfaces of both hands

Allow to dry without wiping

Supervise children under 6 years old

Not recommended for infants

Dispose of wipes in trash after use. Do not flush.

Inactive Ingredient:

Aqua,Glycerin, Propylene Glycol, Aloe Barbadensis Leaf Juice, Decyl Glucoside

PACKAGE LABEL

NDC：74835-012-01

PACKAGE LABEL

NDC：74835-012-02

PACKAGE LABEL

NDC：74835-012-03

PACKAGE LABEL

NDC: 74835-012-04